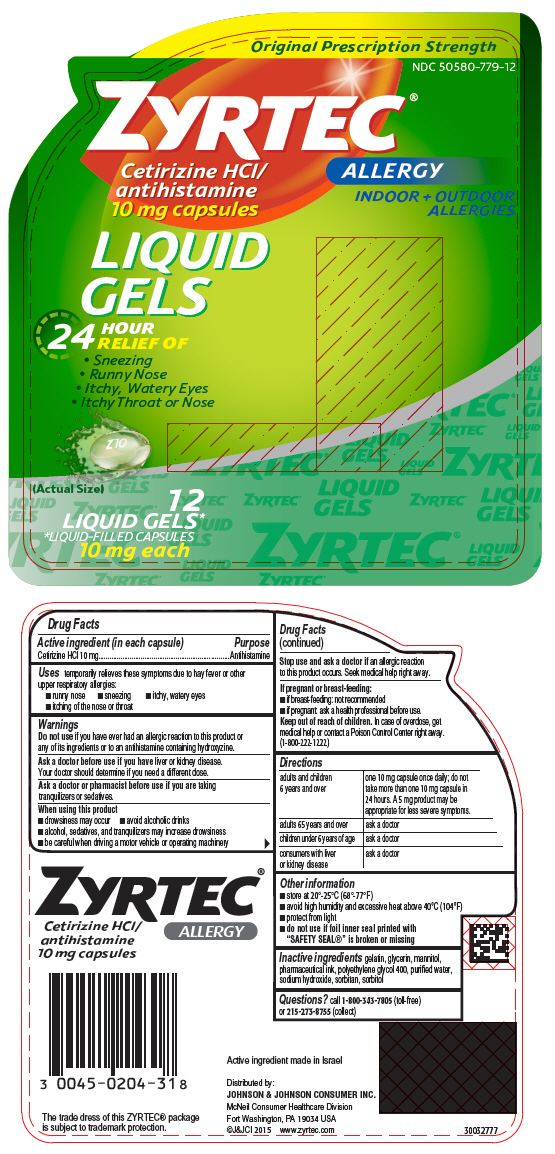 DRUG LABEL: ZYRTEC
NDC: 50580-779 | Form: CAPSULE, LIQUID FILLED
Manufacturer: Kenvue Brands LLC
Category: otc | Type: HUMAN OTC DRUG LABEL
Date: 20241108

ACTIVE INGREDIENTS: CETIRIZINE HYDROCHLORIDE 10 mg/1 1
INACTIVE INGREDIENTS: GELATIN, UNSPECIFIED; GLYCERIN; MANNITOL; POLYETHYLENE GLYCOL 400; WATER; SODIUM HYDROXIDE; SORBITAN; SORBITOL

ZYRTEC

Drug Facts

Active ingredient (in each capsule)

Cetirizine HCl 10 mg

Purpose

Antihistamine

Uses

temporarily relieves these symptoms due to hay fever or other upper respiratory allergies:

- runny nose
- sneezing
- itchy, watery eyes
- itching of the nose or throat

Warnings

Do not use if you have ever had an allergic reaction to this product or any of its ingredients or to an antihistamine containing hydroxyzine.

Ask a doctor before use if you have liver or kidney disease.

Your doctor should determine if you need a different dose.

Ask a doctor or pharmacist before use if you are taking tranquilizers or sedatives.

When using this product

- drowsiness may occur
- avoid alcoholic drinks
- alcohol, sedatives, and tranquilizers may increase drowsiness
- be careful when driving a motor vehicle or operating machinery

Stop use and ask a doctor if an allergic reaction to this product occurs. Seek medical help right away.

If pregnant or breast-feeding

- if breast-feeding: not recommended
- if pregnant: ask a health professional before use.

Keep out of reach of children. In case of overdose, get medical help or contact a Poison Control Center right away. (1-800-222-1222)

Directions

adults and children 6 years and over | one 10 mg capsule once daily; do not take more than one 10 mg capsule in 24 hours. A 5 mg product may be appropriate for less severe symptoms.
adults 65 years and over | ask a doctor
children under 6 years of age | ask a doctor
consumers with liver or kidney disease | ask a doctor

Other information

- store at 20°-25°C (68°-77°F)
- avoid high humidity and excessive heat above 40°C (104°F)
- protect from light
- do not use if foil inner seal printed with "SAFETY SEAL®" is broken or missing

Inactive ingredients

gelatin, glycerin, mannitol, pharmaceutical ink, polyethylene glycol 400, purified water, sodium hydroxide, sorbitan, sorbitol

Questions?

call 1-800-343-7805 (toll-free) or 215-273-8755 (collect)

PRINCIPAL DISPLAY PANEL

Original Prescription Strength

NDC 50580-779-12

ZYRTEC®
ALLERGY

INDOOR + OUTDOOR
ALLERGIES

Cetirizine HCl/
antihistamine
10 mg capsules

LIQUID
GELS

24
HOUR
RELIEF OF

- Sneezing
- Runny Nose
- Itchy, Watery Eyes
- Itchy Throat or Nose

(Actual Size)

12
LIQUID GELS*
*LIQUID-FILLED CAPSULES
10 mg each